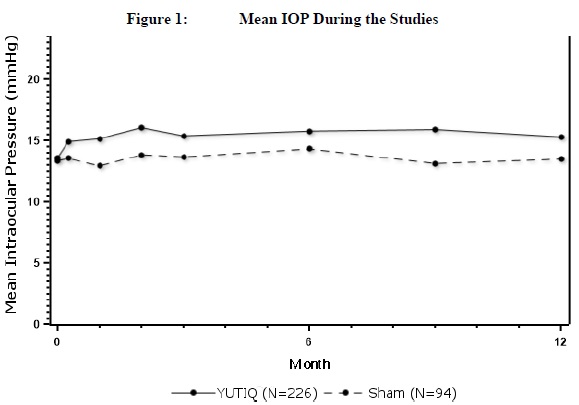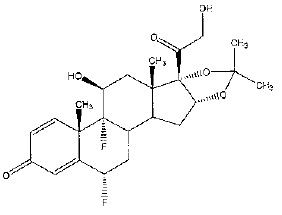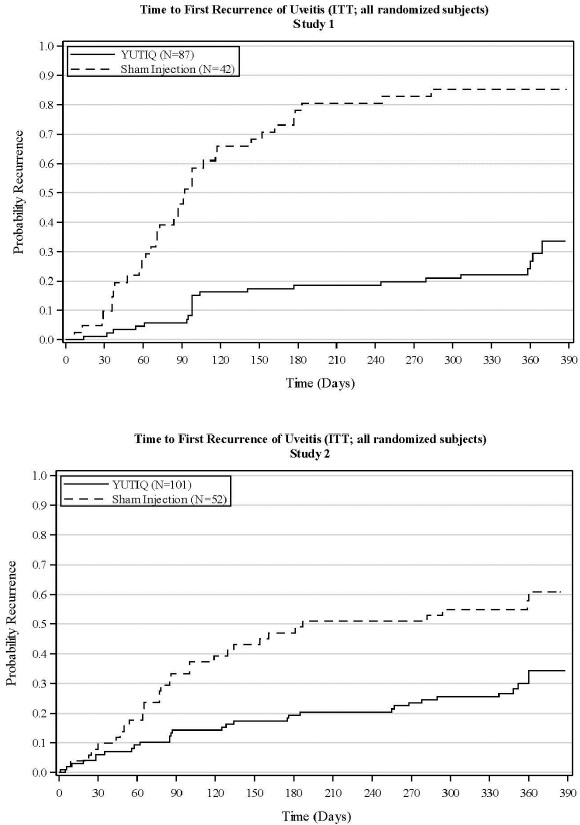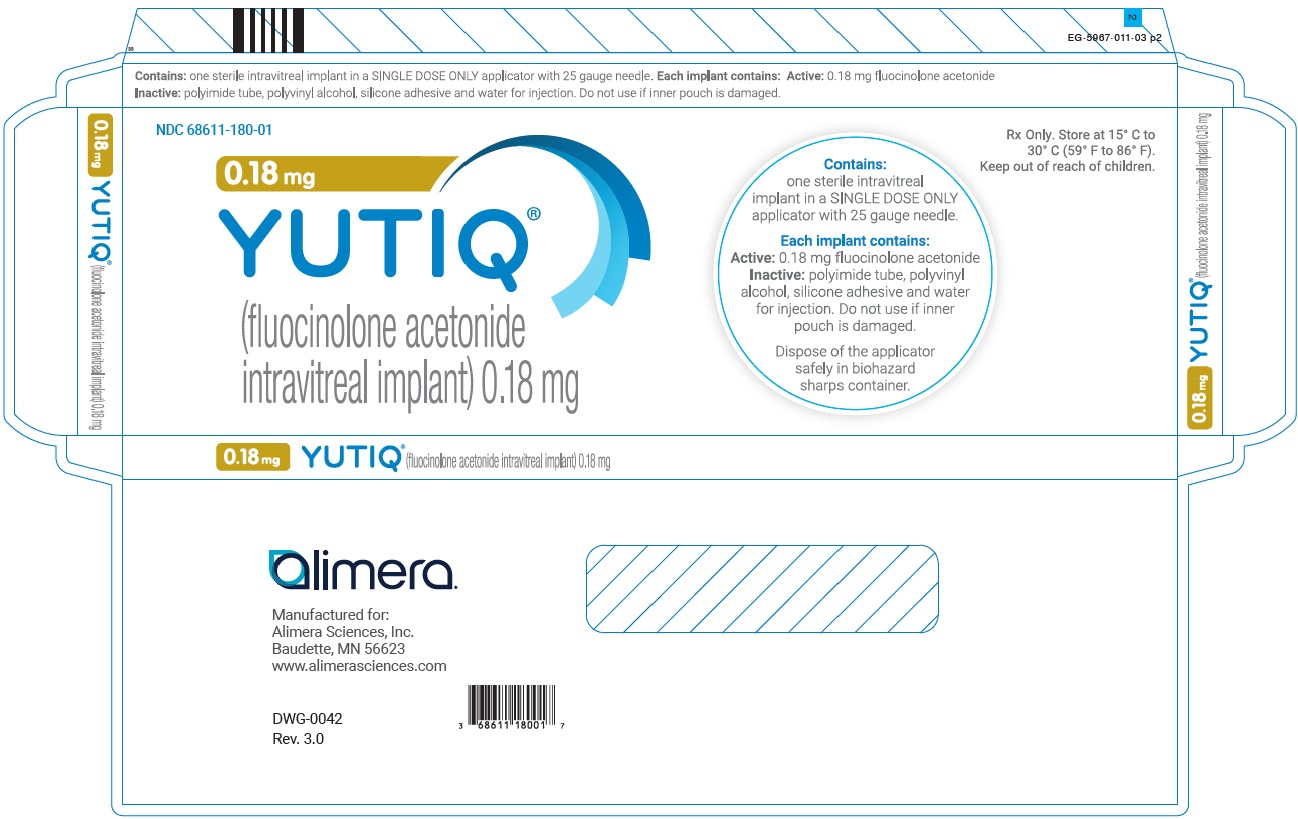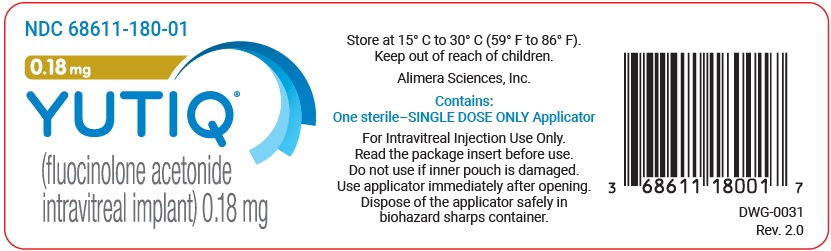 DRUG LABEL: YUTIQ
NDC: 68611-180 | Form: IMPLANT
Manufacturer: ANI Pharmaceuticals, Inc.
Category: prescription | Type: HUMAN PRESCRIPTION DRUG LABEL
Date: 20260219

ACTIVE INGREDIENTS: FLUOCINOLONE ACETONIDE 0.18 mg/1 1
INACTIVE INGREDIENTS: POLYVINYL ALCOHOL, UNSPECIFIED; WATER

HIGHLIGHTS OF PRESCRIBING INFORMATION

These highlights do not include all the information needed to use YUTIQ® safely and effectively. See full prescribing information for YUTIQ.
YUTIQ® (fluocinolone acetonide intravitreal implant) 0.18 mg, for intravitreal injection
Initial U.S. Approval: 1963

1. INDICATIONS AND USAGE

YUTIQ contains a corticosteroid and is indicated for the treatment of chronic non-infectious uveitis affecting the posterior segment of the eye. (1)

2. DOSAGE AND ADMINISTRATION

- For ophthalmic intravitreal injection. (2.1)
- The intravitreal injection procedure should be carried out under aseptic conditions. (2.2)
- Following the intravitreal injection, patients should be monitored for elevation in intraocular pressure and for endophthalmitis. (2.2)

3. DOSAGE FORMS AND STRENGTHS

Non-bioerodible intravitreal implant containing 0.18 mg fluocinolone acetonide in a drug delivery system. (3)

4. CONTRAINDICATIONS

- Ocular or periocular infections (4.1)
- Hypersensitivity (4.2)

5. WARNINGS AND PRECAUTIONS

- Intravitreal injections have been associated with endophthalmitis, eye inflammation, increased intraocular pressure, and retinal detachments. Patients should be monitored following the injection. (5.1)
- Use of corticosteroids may produce posterior subcapsular cataracts, increased intraocular pressure, glaucoma, and may enhance the establishment of secondary ocular infections due to bacteria, fungi, or viruses. (5.2)
- The implant may migrate into the anterior chamber if the posterior lens capsule is not intact. (5.3)

6. ADVERSE REACTIONS

In controlled studies, the most common adverse reactions reported were cataract development and increases in intraocular pressure. (6.1)

To report SUSPECTED ADVERSE REACTIONS, contact Alimera Sciences, Inc. at 1-844-445-8843 or FDA at 1-800-FDA-1088 or www.fda.gov/medwatch.

FULL PRESCRIBING INFORMATION

1. INDICATIONS AND USAGE

YUTIQ® (fluocinolone acetonide intravitreal implant) 0.18 mg is indicated for the treatment of chronic non-infectious uveitis affecting the posterior segment of the eye.

2. DOSAGE AND ADMINISTRATION

2.1. General Dosing Information

For ophthalmic intravitreal injection.

2.2. Administration

The intravitreal injection procedure should be carried out under aseptic conditions, which include use of sterile gloves, a sterile drape, a sterile caliper, and a sterile eyelid speculum (or equivalent). Adequate anesthesia and a broad-spectrum microbicide should be given prior to the injection.

The injection procedure for YUTIQ is as follows:

1. Just prior to injection, administer topical and/or subconjunctival anesthesia at the injection site (inferotemporal quadrant recommended).
2. Administer 2-3 drops of a broad-spectrum microbicide into the lower fornix. The lids may be scrubbed with cotton-tipped applicators soaked with a broad-spectrum microbicide. Place a sterile lid speculum. Have the patient look up and apply additional microbicide solution to the injection site. Allow 30-60 seconds for the topical antiseptic to dry prior to injection of YUTIQ.
3. Optimal placement of YUTIQ is inferior to the optic disc and posterior to the equator of the eye. Measure 4 millimeters inferotemporal from the limbus with the aid of callipers for point of entry into the sclera.
4. Using sterile procedure, open the sterile foil pouch containing YUTIQ.
5. Remove the YUTIQ applicator from the sterile pouch by grasping the barrel of the applicator; do not grasp the plunger.
6. Remove the black plunger stop from the plunger.
7. Carefully remove the protective cap from the needle and inspect the needle tip to ensure it is not bent.
8. Remove the trombone wire from the distal end of the needle. Prior to injection, keep the applicator tip above the horizontal plane to ensure that the YUTIQ implant does not fall out of the applicator.
9. Gently displace the conjunctiva so that after withdrawing the needle, the conjunctival and scleral needle entry sites will not align. Care should be taken to avoid contact between the needle and the lid margin or lashes.
10. Insert the needle through the conjunctiva and sclera up to the positive stop of the applicator.
11. Depress the plunger at the back of the applicator fully to deliver the YUTIQ implant into the back of the eye.
12. Remove the YUTIQ applicator from the eye and discard in biohazard sharps container.
13. Remove the lid speculum and perform indirect ophthalmoscopy to verify adequate central retinal artery perfusion, absence of any other complications, and to verify the placement of the implant. Scleral depression may enhance visualisation of the implant. Immediate measurement of intraocular pressure (IOP) may be performed at the discretion of the ophthalmologist.

Following the injection, patients should be monitored for change in intraocular pressure and for endophthalmitis. Monitoring may consist of a check for perfusion of the optic nerve head immediately after the injection, tonometry within 30 minutes following the injection, and biomicroscopy between two and seven days following the injection. Patients should be instructed to report without delay any symptoms suggestive of endophthalmitis.

3. DOSAGE FORMS AND STRENGTHS

YUTIQ is a non-bioerodible intravitreal implant in a drug delivery system containing 0.18 mg fluocinolone acetonide, designed to release fluocinolone acetonide at an initial rate of 0.25 mcg/day, and lasting 36 months.

4. CONTRAINDICATIONS

4.1. Ocular or Periocular Infections

YUTIQ is contraindicated in patients with active or suspected ocular or periocular infections including most viral disease of the cornea and conjunctiva including active epithelial herpes simplex keratitis (dendritic keratitis), vaccinia, varicella, mycobacterial infections and fungal diseases.

4.2. Hypersensitivity

YUTIQ is contraindicated in patients with known hypersensitivity to any components of this product.

5. WARNINGS AND PRECAUTIONS

5.1. Intravitreal Injection-related Effects

Intravitreal injections, including those with YUTIQ, have been associated with endophthalmitis, eye inflammation, increased or decreased intraocular pressure, and choroidal or retinal detachments. Hypotony has been observed within 24 hours of injection and has resolved within 2 weeks. Patients should be monitored following the intravitreal injection [see Patient Counseling Information (17)].

5.2. Steroid-related Effects

Use of corticosteroids including YUTIQ may produce posterior subcapsular cataracts, increased intraocular pressure and glaucoma. Use of corticosteroids may enhance the establishment of secondary ocular infections due to bacteria, fungi, or viruses.

Corticosteroids are not recommended to be used in patients with a history of ocular herpes simplex because of the potential for reactivation of the viral infection.

5.3. Risk of Implant Migration

Patients in whom the posterior capsule of the lens is absent or has a tear are at risk of implant migration into the anterior chamber.

6. ADVERSE REACTIONS

6.1. Clinical Studies Experience

Because clinical trials are conducted under widely varying conditions, adverse reaction rates observed in the clinical trials of a drug cannot be directly compared to rates in the clinical trials of another drug and may not reflect the rates observed in practice.

Adverse reactions associated with ophthalmic steroids including YUTIQ include cataract formation and subsequent cataract surgery, elevated intraocular pressure, which may be associated with optic nerve damage, visual acuity and field defects, secondary ocular infection from pathogens including herpes simplex, and perforation of the globe where there is thinning of the cornea or sclera.

Studies 1 and 2 were multicenter, randomized, sham injection-controlled, masked trials in which patients with non-infectious uveitis affecting the posterior segment of the eye were treated once with either YUTIQ or sham injection, and then received standard care for the duration of the study. Study 3 was a multicenter, randomized, masked trial in which patients with non-infectious uveitis affecting the posterior segment of the eye were all treated once with YUTIQ, administered by one of two different applicators, and then received standard care for the duration of the study.

Table 1 summarizes data available from studies 1, 2 and 3 through 12 months for study eyes treated with YUTIQ (n=226) or sham injection (n=94). The most common ocular (study eye) and non-ocular adverse reactions are shown in Table 1 and Table 2.

Table 1: Ocular Adverse Reactions Reported in ≥ 1% of Subject Eyes and Non-Ocular Adverse Reactions Reported in ≥ 2% of Patients
Ocular
ADVERSE REACTIONS | YUTIQ (N=226 Eyes) n (%) | Sham Injection (N=94 Eyes) n (%)
Cataract^1 | 63/113 (56%) | 13/56 (23%)
Visual Acuity Reduced | 33 (15%) | 11 (12%)
Macular Edema | 25 (11%) | 33 (35%)
Uveitis | 22 (10%) | 33 (35%)
Conjunctival Hemorrhage | 17 (8%) | 5 (5%)
Eye Pain | 17 (8%) | 12 (13%)
Hypotony Of Eye | 16 (7%) | 1 (1%)
Anterior Chamber Inflammation | 12 (5%) | 6 (6%)
Dry Eye | 10 (4%) | 3 (3%)
Vitreous Opacities | 9 (4%) | 8 (9%)
Conjunctivitis | 9 (4%) | 5 (5%)
Posterior Capsule Opacification | 8 (4%) | 3 (3%)
Ocular Hyperemia | 8 (4%) | 7 (7%)
Vitreous Haze | 7 (3%) | 4 (4%)
Foreign Body Sensation In Eyes | 7 (3%) | 2 (2%)
Vitritis | 6 (3%) | 8 (9%)
Vitreous Floaters | 6 (3%) | 5 (5%)
Eye Pruritus | 6 (3%) | 5 (5%)
Conjunctival Hyperemia | 5 (2%) | 2 (2%)
Ocular Discomfort | 5 (2%) | 1 (1%)
Macular Fibrosis | 5 (2%) | 2 (2%)
Glaucoma | 4 (2%) | 1 (1%)
Photopsia | 4 (2%) | 2 (2%)
Vitreous Hemorrhage | 4 (2%) | 0
Iridocyclitis | 3 (1%) | 7 (7%)
Eye Inflammation | 3 (1%) | 2 (2%)
Choroiditis | 3 (1%) | 1 (1%)
Eye Irritation | 3 (1%) | 1 (1%)
Visual Field Defect | 3 (1%) | 0
Lacrimation Increased | 3 (1%) | 0
Non-ocular
ADVERSE REACTIONS | YUTIQ (N=214 Patients) n (%) | Sham Injection (N=94 Patients) n (%)
Nasopharyngitis | 10 (5%) | 5 (5%)
Hypertension | 6 (3%) | 1 (1%)
Arthralgia | 5 (2%) | 1 (1%)
1. Includes cataract, cataract subcapsular and lenticular opacities in study eyes that were phakic at baseline. 113 of the 226 YUTIQ study eyes were phakic at baseline; 56 of 94 sham-controlled study eyes were phakic at baseline.

Table 2: Summary of Elevated IOP Related Adverse Reactions
ADVERSE REACTIONS | YUTIQ (N=226 Eyes) n (%) | Sham (N=94 Eyes) n (%)
IOP elevation ≥ 10 mmHg from Baseline | 50 (22%) | 11 (12%)
IOP elevation > 30 mmHg | 28 (12%) | 3 (3%)
Any IOP-lowering medication | 98 (43%) | 39 (41%)
Any surgical intervention for elevated IOP | 5 (2%) | 2 (2%)

Figure 1: Mean IOP During the Studies

8. USE IN SPECIFIC POPULATIONS

8.1 Pregnancy

Risk Summary

Adequate and well-controlled studies with YUTIQ have not been conducted in pregnant women to inform drug associated risk. Animal reproduction studies have not been conducted with YUTIQ. It is not known whether YUTIQ can cause fetal harm when administered to a pregnant woman or can affect reproduction capacity. Corticosteroids have been shown to be teratogenic in laboratory animals when administered systemically at relatively low dosage levels. YUTIQ should be given to a pregnant woman only if the potential benefit justifies the potential risk to the fetus.

All pregnancies have a risk of birth defect, loss, or other adverse outcomes. In the United States general population, the estimated background risk of major birth defects and miscarriage in clinically recognized pregnancies is 2% to 4% and 15% to 20%, respectively.

8.2 Lactation

Risk Summary

Systemically administered corticosteroids are present in human milk and can suppress growth and interfere with endogenous corticosteroid production. Clinical or nonclinical lactation studies have not been conducted with YUTIQ. It is not known whether intravitreal treatment with YUTIQ could result in sufficient systemic absorption to produce detectable quantities of fluocinolone acetonide in human milk, or affect breastfed infants or milk production. The developmental and health benefits of breastfeeding should be considered, along with the mother's clinical need for YUTIQ and any potential adverse effects on the breastfed child from YUTIQ.

8.4 Pediatric Use

Safety and effectiveness of YUTIQ in pediatric patients have not been established.

8.5 Geriatric Use

No overall differences in safety or effectiveness have been observed between elderly and younger patients.

11. DESCRIPTION

YUTIQ is a sterile non-bioerodible intravitreal implant containing 0.18 mg fluocinolone acetonide in a 36-month sustained-release drug delivery system. YUTIQ is designed to release fluocinolone acetonide at an initial rate of 0.25 mcg/day. YUTIQ is preloaded into a single-dose applicator to facilitate injection of the implant directly into the vitreous. The drug substance is a synthetic corticosteroid, fluocinolone acetonide.

The chemical name for fluocinolone acetonide is (6α,11β, 16α)-6,9-difluoro-11,21-dihydroxy-16,17-[(1-methylethylidene)bis-(oxy)]-pregna-1,4-diene-3,20-dione. Its chemical structure is:

MW 452.50; molecular formula C24H30F206

Fluocinolone acetonide is a white or almost white, microcrystalline powder, practically insoluble in water, soluble in methanol, ethanol, chloroform and acetone, and sparingly soluble in ether.

Each YUTIQ consists of a light brown 3.5mm x 0.37mm implant containing 0.18 mg of the active ingredient fluocinolone acetonide and the following inactive ingredients: polyimide tube, polyvinyl alcohol, silicone adhesive and water for injection.

12. CLINICAL PHARMACOLOGY

12.1 Mechanism of Action

Corticosteroids inhibit inflammatory responses to a variety of inciting agents including multiple inflammatory cytokines. They inhibit edema, fibrin deposition, capillary dilation, leukocyte migration, capillary proliferation, fibroblast proliferation, deposition of collagen, and scar formation associated with inflammation.

Corticosteroids are thought to act by inhibition of phospholipase A2 via induction of inhibitory proteins collectively called lipocortins. It is postulated that these proteins control biosynthesis of potent mediators of inflammation such as prostaglandins and leukotrienes by inhibiting release of the common precursor, arachidonic acid. Arachidonic acid is released from membrane phospholipids by phospholipase A2.

13. NONCLINICAL TOXICOLOGY

13.1 Carcinogenesis, Mutagenesis, Impairment of Fertility

Long-term animal studies have not been conducted to determine the carcinogenic potential or the effect on fertility of YUTIQ.

Fluocinolone acetonide was not genotoxic in vitro in the Ames test (S. typhimurium and E. coli) and the mouse lymphoma TK assay, or in vivo in the mouse bone marrow micronucleus assay.

14. CLINICAL STUDIES

The efficacy of YUTIQ was assessed in two randomized (2:1, YUTIQ: sham-injection), multi-centre, double-masked, parallel-groups studies (NCT #01694186 and #02746991) that enrolled patients with non-infectious uveitis affecting the posterior segment of the eye. The primary efficacy endpoint in both trials was the proportion of patients who experienced a recurrence of uveitis in the study eye within 6 months of follow-up; recurrence was also assessed at 12 months. Recurrence of uveitis was defined as either deterioration in visual acuity, vitreous haze attributable to non-infectious uveitis or the need for rescue medications.

Table 3: Efficacy Results of Recurrence of Uveitis in Randomized Study Eyes
 | Study 1 |  |  | Study 2
 | YUTIQ N = 87 | Sham N = 42 |  | YUTIQ N = 101 | Sham N = 52
Eyes with recurrence within 6 months, n (%) | 16 (18%) | 33 (79%) |  | 22 (22%) | 28 (54%)
Difference (95% CI) in recurrence rates | 60% (41%, 73%) |  |  | 32% (15%, 48%)
P-value | < 0.01 |  |  | < 0.01
Eyes with recurrence within 12 months, n (%) | 24 (28%) | 36 (86%) |  | 33 (33%) |  | 31 (60%)
Difference (95% CI) in recurrence rates | 58% (40%, 70%) |  |  | 27% (9%, 43%)

Figure 2: Time to First Recurrence of Uveitis (ITT: All Randomized Patients)

16. HOW SUPPLIED/STORAGE AND HANDLING

YUTIQ® (fluocinolone acetonide intravitreal implant) 0.18 mg is supplied in a sterile single-dose preloaded applicator with a 25-gauge needle, packaged in a sealed sterile foil pouch inside a sealed Tyvek pouch inside a carton box.

NDC 68611-180-01

STORAGE AND HANDLING

Storage: Store at 15° C to 30° C (59° F to 86° F).

17. PATIENT COUNSELING INFORMATION

Steroid-related Effects

Advise patients that a cataract may occur after treatment with YUTIQ. If this occurs, advise patients that their vision will decrease, and they will need an operation to remove the cataract and restore their vision.

Advise patients that they may develop increased intraocular pressure with YUTIQ treatment, and the increased IOP may need to be managed with eye drops or surgery.

Intravitreal Injection-related Effects

Advise patients that in the days following intravitreal injection of YUTIQ, they are at risk for potential complications including, but not limited to, the development of endophthalmitis or changes in intraocular pressure.

When to Seek Physician Advice

Advise patients that if the eye becomes red, sensitive to light, painful, or develops a change in vision, they should seek immediate care from an ophthalmologist.

Driving and Using Machines

Inform patients that they may experience temporary visual blurring after receiving an intravitreal injection. Advise patients not to drive or use machines until this has been resolved.

Manufactured For:

Alimera Sciences, Inc.
Baudette, MN 56623
www.alimerasciences.com

Alimera

Manufactured by:

EyePoint US, Inc.
480 Pleasant Street
Watertown, MA 02472 USA
Patented.